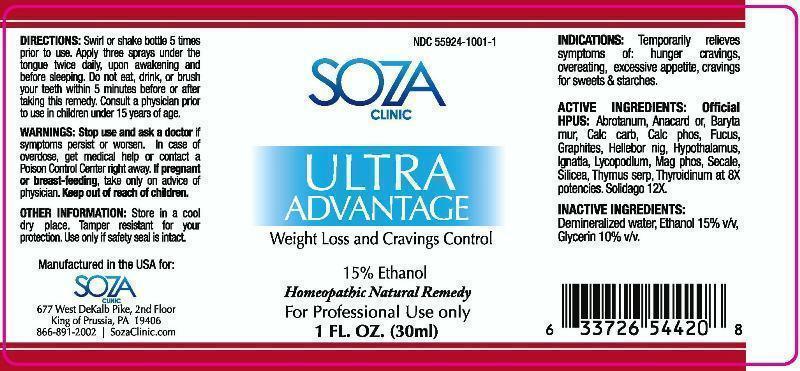 DRUG LABEL: ADVANTAGE
NDC: 55924-1001 | Form: LIQUID
Manufacturer: Soza Clinic
Category: homeopathic | Type: HUMAN OTC DRUG LABEL
Date: 20141215

ACTIVE INGREDIENTS: ARTEMISIA ABROTANUM FLOWERING TOP 8 [hp_X]/1 mL; SEMECARPUS ANACARDIUM JUICE 8 [hp_X]/1 mL; BARIUM CHLORIDE DIHYDRATE 8 [hp_X]/1 mL; OYSTER SHELL CALCIUM CARBONATE, CRUDE 8 [hp_X]/1 mL; TRIBASIC CALCIUM PHOSPHATE 8 [hp_X]/1 mL; FUCUS VESICULOSUS 8 [hp_X]/1 mL; GRAPHITE 8 [hp_X]/1 mL; HELLEBORUS NIGER ROOT 8 [hp_X]/1 mL; SUS SCROFA HYPOTHALAMUS 8 [hp_X]/1 mL; STRYCHNOS IGNATII SEED 8 [hp_X]/1 mL; LYCOPODIUM CLAVATUM SPORE 8 [hp_X]/1 mL; MAGNESIUM PHOSPHATE, DIBASIC TRIHYDRATE 8 [hp_X]/1 mL; CLAVICEPS PURPUREA SCLEROTIUM 8 [hp_X]/1 mL; SILICON DIOXIDE 8 [hp_X]/1 mL; SOLIDAGO VIRGAUREA FLOWERING TOP 12 [hp_X]/1 mL; SUS SCROFA THYROID 8 [hp_X]/1 mL; THYMUS SERPYLLUM 8 [hp_X]/1 mL
INACTIVE INGREDIENTS: WATER; ALCOHOL; GLYCERIN

DRUG FACTS:

ACTIVE INGREDIENTS:

Official HPUS:

ABROTANUM 8X, ANACARDIUM ORIENTALE 8X, BARYTA MURIATICA 8X, CALCAREA CARBONICA 8X, CALCAREA PHOSPHORICA 8X, FUCUS VESICULOSUS 8X, GRAPHITES 8X, HELLEBORUS NIGER 8X, HYPOTHALAMUS (SUIS) 8X, IGNATIA AMARA 8X, LYCOPODIUM CLAVATUM 8X, MAGNESIA PHOSPHORICA 8X, SECALE CORNUTUM 8X, SILICEA 8X, SOLIDAGO VIRGAUREA 12X, THYROIDINUM (SUIS) 8X, THYMUS SERPYLLUM 8X

INDICATIONS:

Temporarily relieves symptoms of: hunger cravings, overeating, excessive appetite, cravings for sweets & starches.

WARNINGS:

Stop use and ask a doctor if symptoms persist or worsen. In case of overdose, get medical help or contact a Poison Control Center right away.

If pregnant or breast-feeding, take only on advice of physician.

Keep out of reach of children.

KEEP OUT OF REACH OF CHILDREN:

DIRECTIONS:

Swirl or shake bottle 5 times prior to use. Apply three sprays under the tongue twice daily, upon awakening and before sleeping. Do not eat, drink or brush your teeth within 5 minutes before or after taking this remedy. Consult a physician prior to use in children under 15 years of age.

INDICATIONS:

Temporarily relieves symptoms of: hunger cravings, overeating, excessive appetite, cravings for sweets & starches.

INACTIVE INGREDIENTS:

Demineralized water, Ethanol 15% v/v, Glycerin 10% v/v.

QUESTIONS:

Manufactured in the USA for:

SOZA CLINIC

677 West DeKalb Pike, 2nd Floor

King of Prussia, PA 19406

866-891-2002 SozaClinic.com

PACKAGE LABEL DISPLAY:

NDC 55924-1001-1

SOZA

CLINIC

ULTRA

ADVANTAGE

Weight Loss and Cravings Control

Homeopathic Natural Remedy

For Professional Use only

1 FL. OZ. (30ml)